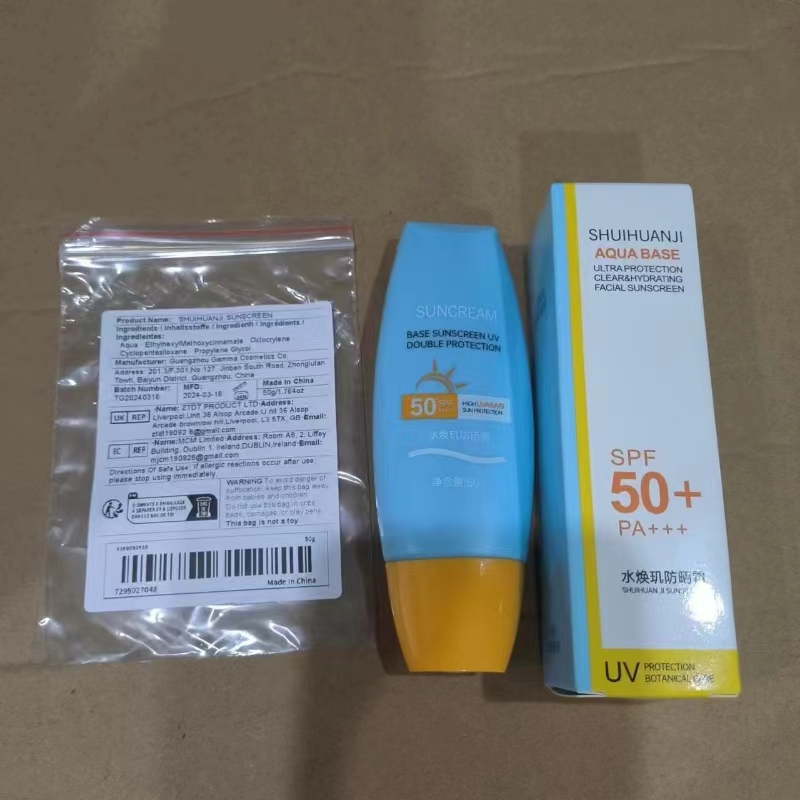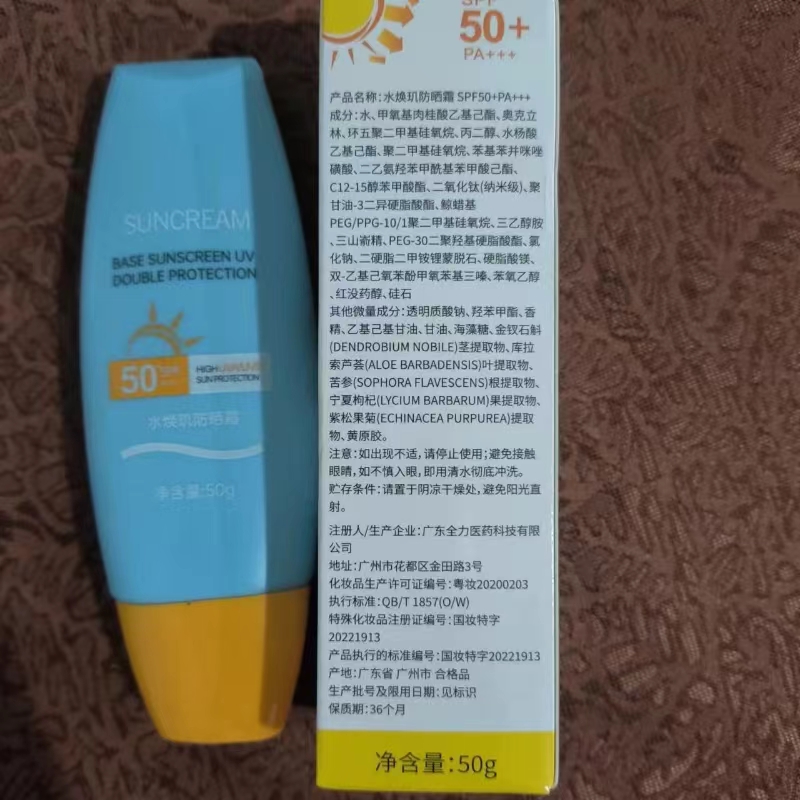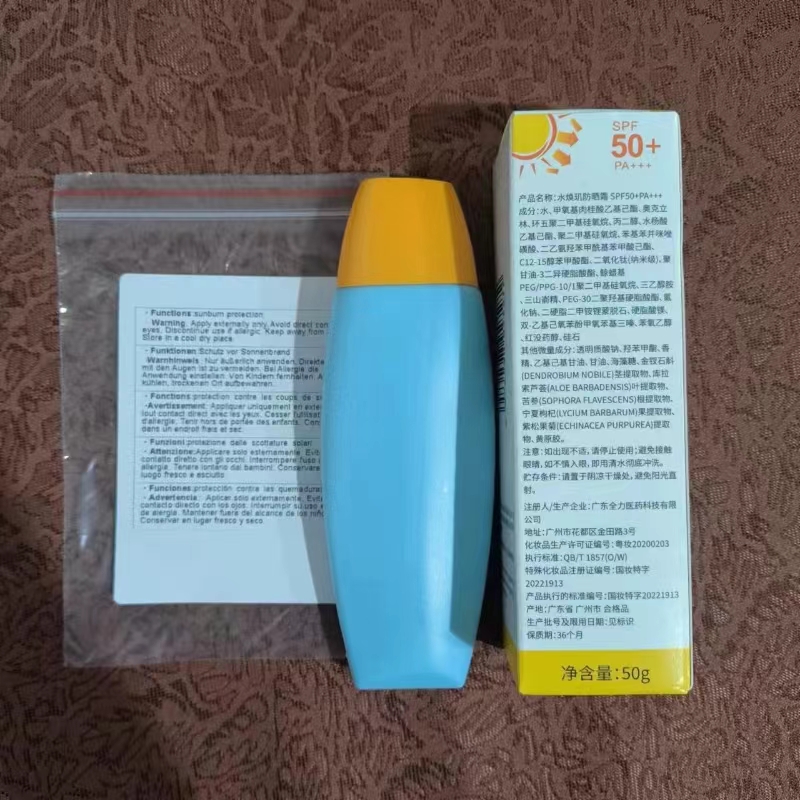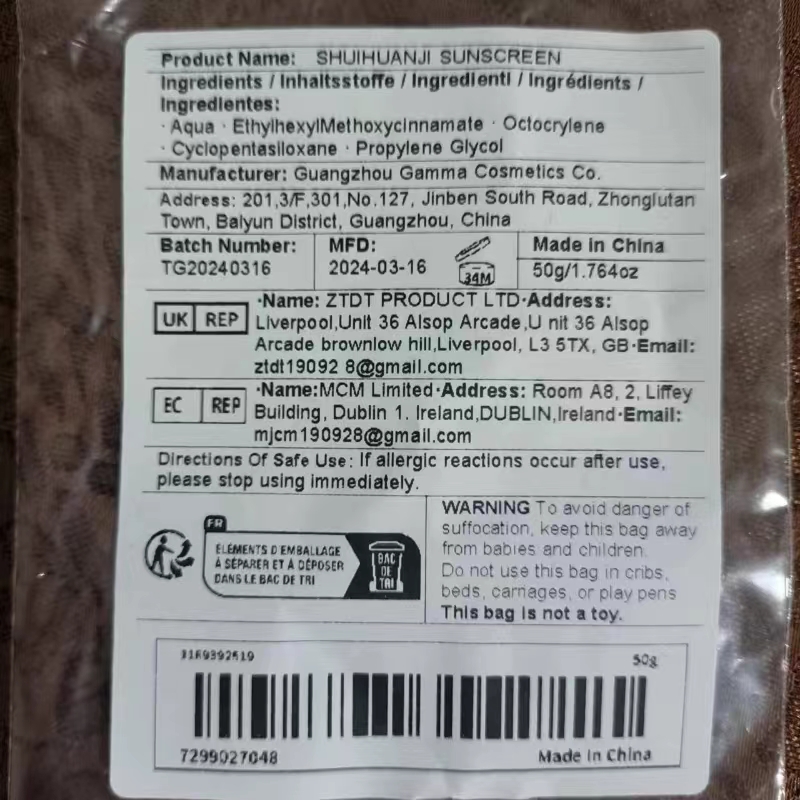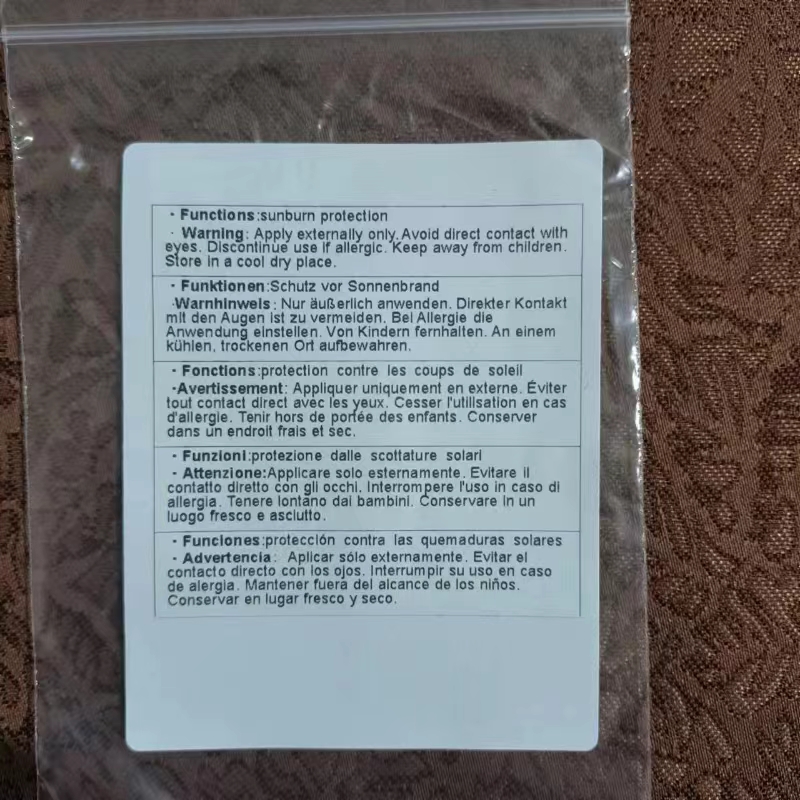 DRUG LABEL: SHUIHUANJI SUNSCREEN
NDC: 84487-001 | Form: CREAM
Manufacturer: Ruian Information Technology (Guangdong) Co., Ltd.
Category: otc | Type: HUMAN OTC DRUG LABEL
Date: 20240702

ACTIVE INGREDIENTS: ETHYL METHOXYCINNAMATE 200 mg/1 g; DIMETHICONE CROSSPOLYMER (450000 MPA.S AT 12% IN CYCLOPENTASILOXANE) 100 mg/1 g; OCTOCRYLENE 80 mg/1 g
INACTIVE INGREDIENTS: DIMETHICONE 50 mg/1 g; PROPYLENE GLYCOL 1-MYRISTATE 50 mg/1 g

Active ingredients

ETHYLHEXYL METHOXYCINNAMATE 6.5%
OCTOCRYLENE 5%
CYCLOPENTASILOXANE 6%

Purpose
Sunscreen
Moisturizes throughout theday & helps protects

Uses
Apply sunscreen generously to exposedskin. Rub it in evenly. Reapply as neededespecially after swimming or sweating.Enjoy your sun-protected day!

Warnings
For exteral use only.

Do not use on damaged or broken skin.

When using this product
Only for external use. do not ingest.
Avoid direct contact with eyes.

Stop use and ask a doctor if rash occurs.

Keep out of reach of children.
if swallowed, get medical help or contact a Poison Control Center right away.

Ask Doctor When Pregnant or breast-feeding.

DOSAGE AND ADMINISTRATION

Directions for use
-apply liberally 15 minutes before sun exposure.
-reapply at least every 2 hours.
-use a water resistant sunscreen if swimming or sweating.
-Sun Protection Measures: Spending time in the sun increases your risk of skin cancer and early skin aging
-Spectrum SPF value of 15 or higher and other sun protection：
-limit time in the sun, especially from 10 a.m.-2 p.m.
-and wear long-sleeved shirts, pants, hats, and sunglasses.

Other information
Before use, read all information on the carton.
Store at controlled room temperature20 to 25 C (68 to 77°F)

Inactive ingredients

Water, Sodium Chloride, Lithium Montmorillonite, Magnesium Stearate, Resveratrol, Silica, Sodium Hyaluronate, Glycerol, Trehalose, Aloe Vera Leaf Extract, Sophora Flavescens Root Extract

Additional Ingredients(Fragrances,Stabilizers,etc.)

Hydroxybenzene Methyl Ester, Xanthan Gum